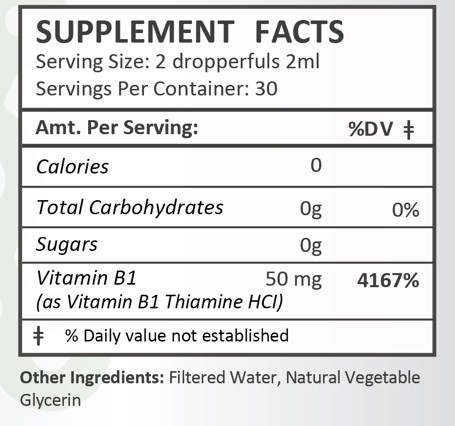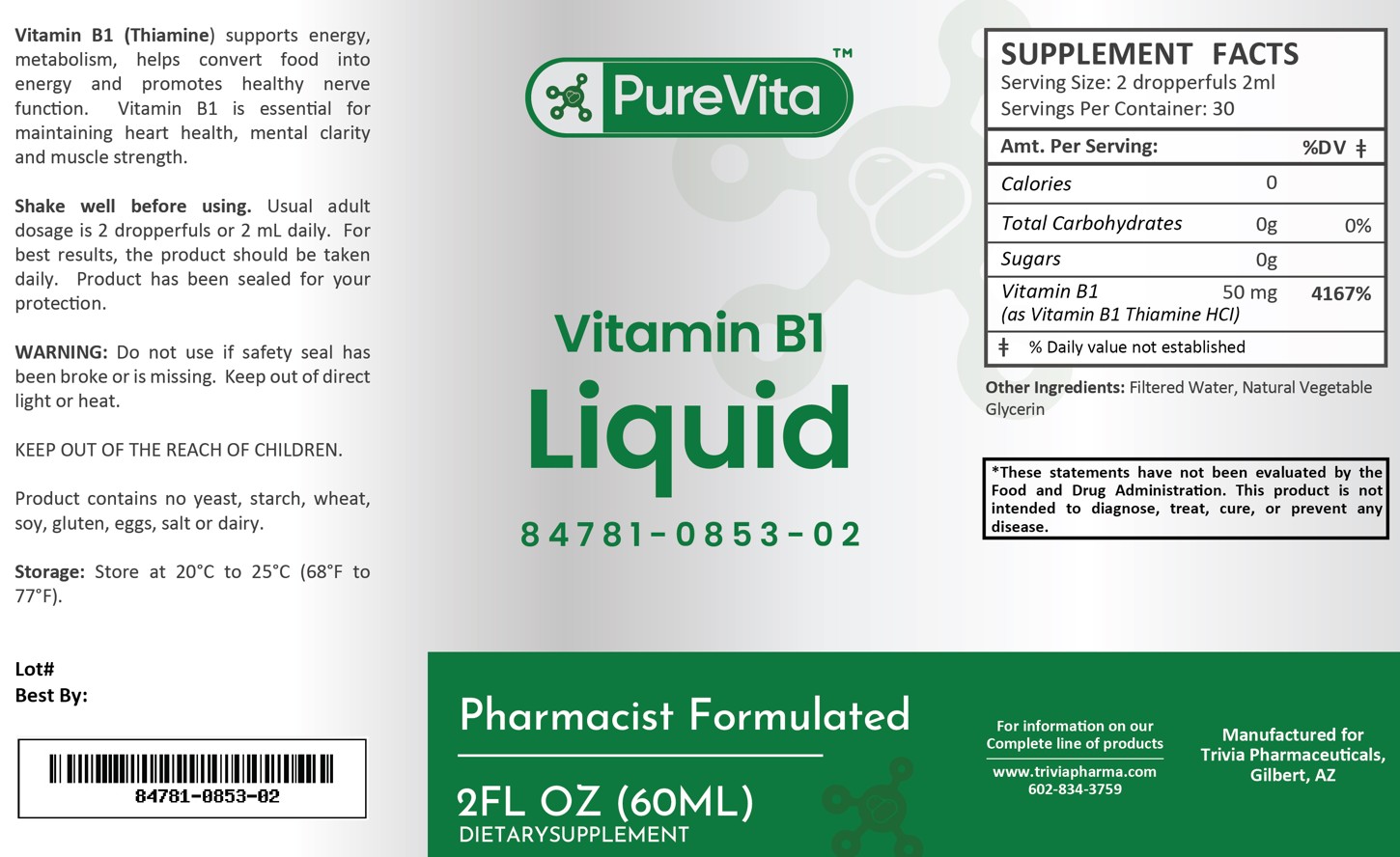 DRUG LABEL: PureVita Vitamin B1
NDC: 84781-853 | Form: LIQUID
Manufacturer: Trivia Pharmaceuticals
Category: other | Type: Dietary Supplement
Date: 20250225

ACTIVE INGREDIENTS: THIAMINE 50 mg/2 mL

PureVita Vitamin B1

Health Claim:

Vitamin B1 50 mg/2 mL Dropper

Description:

PureVita Vitamin B1 supports energy, metabolism, helps convert food into energy and promotes healthy nerve function. Vitamin B1 is essential for maintaining heart health, mental clarity and muscle strength.

This listed product is not a National Drug Code, but instead has merely been formatted to comply with standard industry practice for pharmacy and insurance computer systems.

Warnings:

Do not use if safety seal has been broken or is missing. Keep out of direct light or heat.

KEEP OUT OF THE REACH OF CHILDREN.

Product contains no yeast, starch, wheat, soy, gluten, eggs, salt or dairy.

Dosage and Administration:

Usual adult dose is 2 dropperfuls or 2 mL daily. For the best results, the product should be taken daily. Product has been sealed for your protection.

PRECAUTIONS

PureVita Vitamin B1 is supplied as clear, white liquid

84781-0853-02

Reserved for Professional Recommendation

All prescriptions using this product shall be pursuant to state statutes as applicable. This is not an Orange Book product. There are no implied or explicit claims on therapeutic equivalence.

Manufactured for:
Trivia Pharmaceuticals

Gilbert, AZ

Storage:

Storage: Store at 20oC to 25oC (68oF to 77oF). Keep refrigerated after opening.